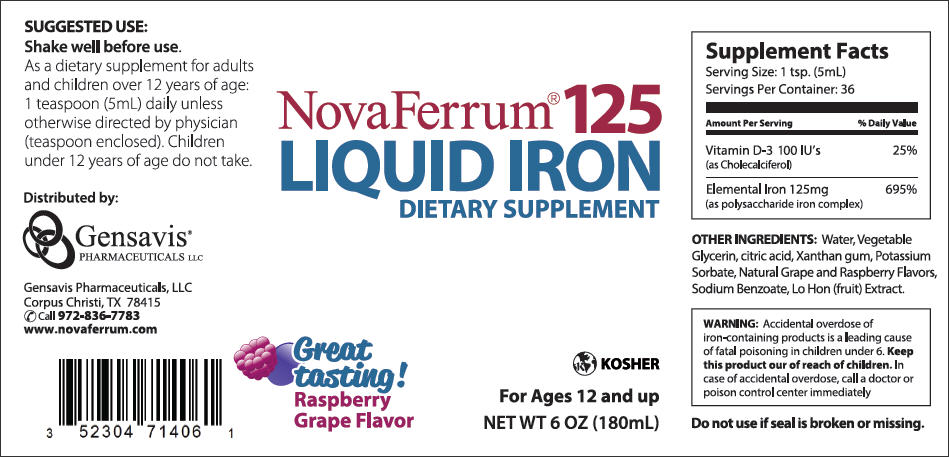 DRUG LABEL: NovaFerrum 
NDC: 52304-714 | Form: LIQUID
Manufacturer: Gensavis Pharmaceuticals, LLC
Category: other | Type: DIETARY SUPPLEMENT
Date: 20131031

ACTIVE INGREDIENTS: iron 125 mg/5 mL; CHOLECALCIFEROL 100 [iU]/5 mL
INACTIVE INGREDIENTS: water; Citric Acid Monohydrate; Xanthan Gum; Potassium Sorbate; Sodium Benzoate; SIRAITIA GROSVENORII FRUIT

NovaFerrum 125
Liquid Iron Dietary Supplement

STATEMENT OF IDENTITY

Supplement Facts

Serving Size: 1 tsp. (5mL)
Servings Per Container: 36

Amount Per Serving | % Daily Value
Vitamin D-3 100 IU's (as Cholecalciferol) | 25%
Elemental Iron 125mg (as polysaccharide iron complex) | 695%

HEALTH CLAIM

OTHER INGREDIENTS: Water, Vegetable Glycerin, citric acid, Xanthan gum, Potassium Sorbate, Natural Grape and Raspberry Flavors, Sodium Benzoate, Lo Hon (fruit) Extract.

WARNING

Accidental overdose of iron-containing products is a leading cause of fatal poisoning in children under 6. Keep this product our of reach of children. In case of accidental overdose, call a doctor or poison control center immediately.

Do not use if seal is broken or missing.

Suggested use

Shake well before use.

As a dietary supplement for adults and children over 12 years of age: 1 teaspoon (5mL) daily unless otherwise directed by physician (teaspoon enclosed). Children under 12 years of age do not take.

WARNINGS

WARNING: If you are pregnant or lactating, consult your physician before using this product.

Distributed by:
Gensavis Pharmaceuticals, LLC
Corpus Christi, TX 78415
Call 972-836-7783
www.novaferrum.com

PRINCIPAL DISPLAY PANEL - 180mL Bottle Label

NovaFerrum 125
Liquid Iron Dietary Supplement

KOSHER
For Ages 12 and up
NET WT 6 OZ (180mL)

Great tasting!
Raspberry Grape Flavor